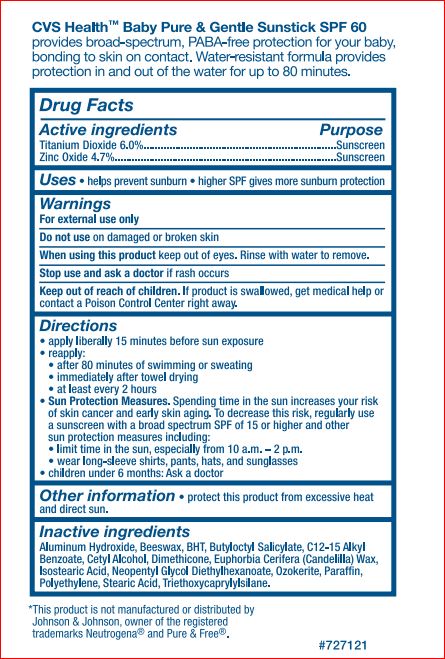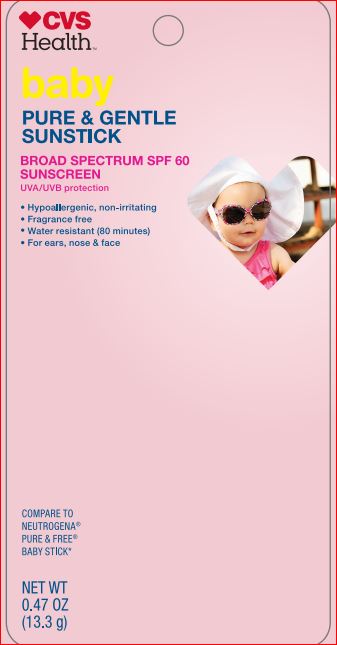 DRUG LABEL: Baby Pure Gentle SunStick SPF 60
NDC: 59779-270 | Form: STICK
Manufacturer: CVS
Category: otc | Type: HUMAN OTC DRUG LABEL
Date: 20171222

ACTIVE INGREDIENTS: TITANIUM DIOXIDE 6 g/100 g; Zinc Oxide 4.7 g/100 g
INACTIVE INGREDIENTS: ALUMINUM HYDROXIDE; YELLOW WAX; BUTYLATED HYDROXYTOLUENE; BUTYLOCTYL SALICYLATE; ALKYL (C12-15) BENZOATE; CETYL ALCOHOL; DIMETHICONE; CANDELILLA WAX; ISOSTEARIC ACID; NEOPENTYL GLYCOL DIETHYLHEXANOATE; CERESIN; PARAFFIN; HIGH DENSITY POLYETHYLENE; STEARIC ACID; TRIETHOXYCAPRYLYLSILANE

Active Ingredients

Titanium Dioxide 6.0%

Zinc Oxide 4.7%

PURPOSE

SUnscreen

Uses:

helps prevent sunburn

Warnings:

For external use only

Do not use on damaged or broken skin. When using this product keep out of eyes. Rinse with water to remove. Stop use and ask a doctor if rash occurs.

Keep out of reach of children.

If product is swallowedm ger medical help or contact a Posion Control Center right away.

Directions:

- apply liberally 15 minutes before sun exposure
- reapply:
- after 80 minutes of swimming or sweating
- immediately after towel drying
- at least every 2 hours

Sun Protection Measure. Spending Time in the sun increases your risk of skin cancer and early aging. To decrease this risk, regularly use a sunscreen with a broad spectrum SPF of 15 or higher and other sun protection measures including:

- limit time in the sun, especially from 10 a.m.-2 p.m.
- wear long-sleeve shirts, pants, hats, and sunglasses
- children under 6 months: Ask a doctor

Other information

- protect this product from excessive heat and direct sun.

PACKAGE LABEL

CVS

pharmacy

BABY

PURE & GENTLE

SUNSTICK

BROAD SPECTRUM SPF 60

UVA/UVB protection

Sunscreen

Fragrance free

Hypoallergenic, non-irritating

Water resistant (80 minutes)

For ears, nose & face

COMPARE TO NEUTROGENA

PURE & FREE BABY STICK

NET WT 0.47 OZ (13.3 g)